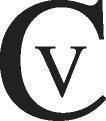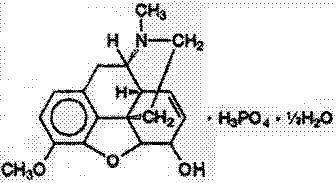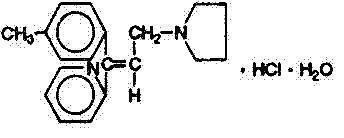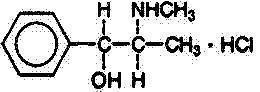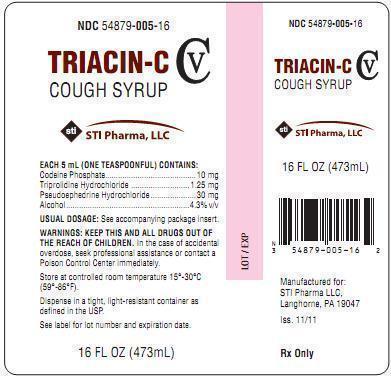 DRUG LABEL: Triacin-C
NDC: 54879-005 | Form: SYRUP
Manufacturer: STI Pharma LLC
Category: prescription | Type: HUMAN PRESCRIPTION DRUG LABEL
Date: 20150728
DEA Schedule: CV

ACTIVE INGREDIENTS: TRIPROLIDINE HYDROCHLORIDE 1.25 mg/5 mL; PSEUDOEPHEDRINE HYDROCHLORIDE 30 mg/5 mL; CODEINE PHOSPHATE 10 mg/5 mL
INACTIVE INGREDIENTS: METHYLPARABEN; SODIUM BENZOATE; ALCOHOL; SACCHARIN SODIUM; SORBITOL; GLYCERIN; ANHYDROUS CITRIC ACID; SODIUM CITRATE; CARAMEL; WATER

TRIACIN-C (Triprolidine HCl, Pseudoephedrine HCl, and Codeine Phosphate Syrup)

BOXED WARNING

WARNING: Death Related to Ultra-Rapid Metabolism of Codeine to Morphine Respiratory depression and death have occurred in children who received codeine following tonsillectomy and/or adenoidectomy and had evidence of being ultra-rapid metabolizers of codeine due to a CYP2D6 polymorphism (see WARNINGS - Codeine Phosphate - Death Related to Ultra-Rapid Metabolism of Codeine to Morphine).

DESCRIPTION

Each 5 mL (one teaspoonful) of syrup for oral administration contains:

Codeine Phosphate……10 mg

WARNING: May be habit forming.

Triprolidine Hydrochloride……1.25 mg

Pseudoephedrine Hydrochloride……30 mg

Alcohol 4.3%.

Inactive ingredients: sodium benzoate, methylparaben, sodium saccharin, sorbitol, glycerin, citric acid, sodium citrate, caramel flavor and USP purified water.

Triacin-C produces antitussive, antihistaminic and nasal decongestant effects. The components have the following chemical names and structural formulas:

Codeine Phosphate, USP

7,8-didehydro-4,5 α-epoxy-3-methoxy-17-methylmorphinan-6α-ol phosphate (1:1) (salt) hemihydrate

Triprolidine Hydrochloride, USP

(E)-2-[3(1-Pyrrolidinyl)-1-p-tolylpropenyl]pyridine monohydrochloride monohydrate

Pseudoephedrine Hydrochloride, USP

Benzenemethanol, α-[1-(methylamino)ethyl]-,[S-(R*, R*)]- hydrochloride

CLINICAL PHARMACOLOGY

Codeine: Codeine probably exerts its antitussive activity by depressing the medullary (brain) cough center, thereby raising its threshold for incoming cough impulses.

Codeine is readily absorbed from the gastrointestinal tract, with a therapeutic dose reaching peak antitussive effectiveness in about 2 hours and persisting for 4 to 6 hours. Codeine is rapidly distributed from blood to body tissues and taken up preferentially by parenchymatous organs such as liver, spleen and kidney. It passes the blood brain barrier and is found in fetal tissue and breast milk.

The drug is not bound by plasma proteins nor is it accumulated in body tissues. Codeine is metabolized in the liver to morphine and norcodeine, each representing about 10 percent of the administered codeine dose. About 90 percent of the dose is excreted within 24 hours, primarily through the kidneys. Urinary excretion products are free and glucuronide-conjugated codeine (about 70%), free and conjugated norcodeine (about 10%), free and conjugated morphine (about 10%), normorphine (under 4%) and hydrocodone (<1%). The remainder of the dose appears in the feces.

Triprolidine: Antihistamines such as triprolidine hydrochloride act as antagonists of the H1 histamine receptor. Consequently, they prevent histamine from eliciting typical immediate hypersensitivity responses in the nose, eyes, lungs and skin.

Animal distribution studies have shown localization of triprolidine in lung, spleen and kidney tissue. Liver microsome studies have revealed the presence of several metabolites with an oxidized product of the toluene methyl group predominating.

Pseudoephedrine: Pseudoephedrine acts as an indirect sympathomimetic agent by stimulating sympathetic (adrenergic) nerve endings to release norepinephrine. Norepinephrine in turn stimulates alpha and beta receptors throughout the body. The action of pseudoephedrine hydrochloride is apparently more specific for the blood vessels of the upper respiratory tract and less specific for the blood vessels of the systemic circulation. The vasoconstriction elicited at these sites results in the shrinkage of swollen tissues in the sinuses and nasal passages.

Pseudoephedrine is rapidly and almost completely absorbed from the gastrointestinal tract. Considerable variation in half-life has been observed (from about 4½ to 10 hours), which is attributed to individual differences in absorption and excretion. Excretion rates are also altered by urine pH, increasing with acidification and decreasing with alkalinization. As a result, mean half-life falls to about 4 hours at pH 5 and increases to 12 to 13 hours at pH 8.

After administration of a 60 mg tablet, 87 to 96% of the pseudoephedrine is cleared from the body within 24 hours. The drug is distributed to body tissues and fluids, including fetal tissue, breast milk and the central nervous system (CNS). About 55 to 75% of an administered dose is excreted unchanged in the urine; the remainder is apparently metabolized in the liver to inactive compounds by N-demethylation, parahydroxylation and oxidative deamination.

PRECAUTIONS

General: Triacin-C should be prescribed with caution for certain special-risk patients, such as the elderly or debilitated, and for those with severe impairment of renal or hepatic function, gallbladder disease or gallstones, respiratory impairment, cardiac arrhythmias, history of bronchial asthma, prostatic hypertrophy or urethral stricture, and in patients known to be taking other antitussive, antihistamine or decongestant medications. Patients’ self-medication habits should be investigated to determine their use of such medications. Triacin-C is intended for short-term use only.

Information For Patients:
Advise patients that some people have a genetic variation that results in codeine changing into morphine more rapidly and completely than other people. Most people are unaware of whether they are an ultra-rapid codeine metabolizer or not. These higher-than-normal levels of morphine in the blood may lead to life-threatening or fatal respiratory depression or signs of overdose such as extreme sleepiness, confusion, or shallow breathing. Children with this genetic variation who were prescribed codeine after tonsillectomy and/or adenoidectomy for obstructive sleep apnea may be at greatest risk based on reports of several deaths in this population due to respiratory depression. As a result, codeine is contraindicated in all children who undergo tonsillectomy and/or adenoidectomy. Advise caregivers of children receiving codeine for other reasons to monitor for signs of respiratory depression (see WARNINGS – Death Related to Ultra-Rapid metabolism of Codeine to Morphine).
1. Patients should be warned about engaging in activities requiring mental alertness such as driving a car, operating dangerous machinery or hazardous appliances.
2. Patients with a history of glaucoma, peptic ulcer, urinary retention or pregnancy should be cautioned before starting this product.
3. Patients should be told not to take alcohol, sleeping pills, sedatives or tranquilizers while taking Triacin-C.
4. Antihistamines may cause dizziness, drowsiness, dry mouth, blurred vision, weakness, nausea, headache or nervousness in some patients.
5. Patients should be told to store this medicine in a tightly closed container in a dry, cool place away from heat or direct sunlight and out of the reach of children.
6. Nursing Mothers – refer to following section titled “Nursing Mothers.” (see WARNINGS – Death Related to Ultra-Rapid Metabolism of Codeine to Morphine).

This product should not be used by persons intolerant to sympathomimetics used for the relief of nasal or sinus congestion. Such drugs include ephedrine, epinephrine, phenylephrine and phenylpropanolamine. Symptoms of intolerance include drowsiness, dizziness, weakness, difficulty in breathing, tenseness, muscle tremors or palpitations.

Codeine may be habit-forming when used over long periods or in high doses. Patients should take the drug only for as long, in the amounts, and as frequently as prescribed.

Drug Interactions: Triacin-C may enhance the effects of:

1. Monoamine oxidase (MAO) inhibitors;
2. other narcotic analgesics, alcohol, general anesthetics, tranquilizers, sedative-hypnotics, surgical skeletal muscle relaxants, or other CNS depressants, by causing increased CNS depression.

This product may diminish the antihypertensive effects of guanethidine, bethanidine, methyldopa and reserpine.

Drug/Laboratory Test Interactions: Codeine: Narcotic administration may increase serum amylase levels.

Carcinogenesis, Mutagenesis, Impairment Of Fertility: No adequate studies have been conducted in animals to determine whether the components of Triacin-C have a potential for carcinogenesis, mutagenesis or impairment of fertility.

Pregnancy: Teratogenic Effects – Pregnancy category C. Animal reproduction studies have not been conducted with Triacin-C. It is also not known whether this product can cause fetal harm when administered to a pregnant woman or can affect reproduction capacity. This product should be given to a pregnant woman only if clearly needed.

Teratology studies have been conducted with the three ingredients of Triacin-C. Pseudoephedrine studies were conducted in rats at doses up to 150 times the human dose; triprolidine was studied in rats and rabbits at doses up to 125 times the human dose, and codeine studies were conducted in rats and rabbits at doses up to 150 times the human dose. No evidence of teratogenic harm to the fetus was revealed in any of these studies. However, overt signs of toxicity were observed in the dams which received pseudoephedrine. This was reflected in reduced average weight and length and rate of skeletal ossification in their fetuses.

Nursing Mothers: The components of Triacin-C are excreted in breast milk in small amounts, but the significance of their effects on nursing infants is not known. Because of the potential for serious adverse reactions in nursing infants from maternal ingestion of this product, a decision should be made whether to discontinue nursing or to discontinue the drug, taking into account the importance of the drug to the mother. (see WARNINGS – Death Related to Ultra-Rapid Metabolism of Codeine to Morphine).

Pediatric Use: Respiratory depression and death have occurred in children with obstructive sleep apnea who received codeine in the post-operative period following tonsillectomy and/or adenoidectomy and had evidence of being ultra-rapid metabolizers of codeine (i.e., multiple copies of the gene for cytochrome P450 isoenzyme CYP2D6 or high morphine concentrations). These children may be particularly sensitive to the respiratory depressant effects of codeine that has been rapidly metabolized to morphine. Codeine is contraindicated for post-operative pain management in these patients (see WARNINGS - Death Related to Ultra-Rapid Metabolism of Codeine to Morphine and CONTRAINDICATIONS)

As in adults, the combination of an antihistamine, sympathomimetic amine and codeine can elicit either mild stimulation or mild sedation in pediatric patients. In pediatric patients particularly, the ingredients in this drug product in overdosage may produce hallucinations, convulsions and death. Symptoms of toxicity in pediatric patients may include fixed dilated pupils, flushed face, dry mouth, fever, excitation, hallucinations, ataxia, incoordination, athetosis, tonic clonic convulsions and postictal depression, (see CONTRAINDICATIONS and OVERDOSAGE sections).

Use In Elderly (Approximately 60 Years Or Older): The ingredients in Triacin-C are more likely to cause adverse reactions in elderly patients.

INDICATIONS AND USAGE

Triacin-C is indicated for temporary relief of coughs and upper respiratory symptoms, including nasal congestion, associated with allergy or the common cold.

CONTRAINDICATIONS

Triacin-C is contraindicated under the following conditions:

Codeine sulfate is contraindicated for postoperative pain management in children who have undergone tonsillectomy and/or adenoidectomy.

Use In Newborn or Premature Infants

This drug should not be used in newborn or premature infants.

Use In Lower Respiratory Disease

Antihistamines should not be used to treat lower respiratory tract symptoms, including asthma.

Hypersensitivity To (1) codeine phosphate or other narcotics; (2) triprolidine hydrochloride or other antihistamines of similar chemical structure; or (3) sympathomimetic amines, including pseudoephedrine.

Sympathomimetic amines are contraindicated in patients with severe hypertension, severe coronary artery disease and in patients on monoamine oxidase (MAO) inhibitor therapy (see PRECAUTIONS - Drug Interactions).

WARNINGS

Deaths Related to Ultra-Rapid Metabolism of Codeine to Morphine

Respiratory depression and death have occurred in children who received codeine in the postoperative period following tonsillectomy and/or adenoidectomy and had evidence of being ultrarapid metabolizers of codeine (i.e., multiple copies of the gene for cytochrome P450 isoenzyme 2D6 or high morphine concentrations). Deaths have also occurred in nursing infants who were exposed to high levels of morphine in breast milk because their mothers were ultra-rapid metabolizers of codeine (see PRECAUTIONS-Nursing Mothers).

Some individuals may be ultra-rapid metabolizers because of a specific CYP2D6 genotype (gene duplications denoted as *1/*1xN or *1/*2xN). The prevalence of this CYP2D6 phenotype varies widely and has been estimated at 0.5 to 1% in Chinese and Japanese, 0.5 to 1% in Hispanics, 1 to 10% in Caucasians, 3% in African Americans, and 16 to 28% in North Africans, Ethiopians, and Arabs. Data are not available for other ethnic groups. These individuals convert codeine into its active metabolite, morphine, more rapidly and completely than other people. This rapid conversion results in higher than expected serum morphine levels. Even at labeled dosage regimens, individuals who are ultra-rapid metabolizers may have life-threatening or fatal respiratory depression or experience signs of overdose (such as extreme sleepiness, confusion, or shallow breathing) (see OVERDOSAGE).

Children with obstructive sleep apnea who are treated with codeine for post-tonsillectomy and/or adenoidectomy pain may be particularly sensitive to the respiratory depressant effects of codeine that has been rapidly metabolized to morphine. Codeine is contraindicated for post-operative pain management in all pediatric patients undergoing tonsillectomy and/or adenoidectomy (see CONTRAINDICATIONS).

When prescribing codeine-containing drugs, healthcare providers should choose the lowest effective dose for the shortest period of time and inform patients and caregivers about these risks and the signs of morphine overdose.

Triacin-C should be used with considerable caution in patients with increased intraocular pressure (narrow angle glaucoma), stenosing peptic ulcer, pyloroduodenal obstruction, symptomatic prostatic hypertrophy, bladder neck obstruction, hypertension, diabetes mellitus, ischemic heart disease, and hyperthyroidism.

In the presence of head injury or other intracranial lesions, the respiratory depressant effects of codeine and other narcotics may be markedly enhanced, as well as their capacity for elevating cerebrospinal fluid pressure.

Narcotics also produce other CNS depressant effects, such as drowsiness, that may further obscure the clinical course of patients with head injuries.

Codeine or other narcotics may obscure signs on which to judge the diagnosis or clinical course of patients with acute abdominal conditions.

ADVERSE REACTIONS

(The most frequent adverse reactions are underlined.)

General: Dryness of mouth, dryness of nose, dryness of throat, urticaria, drug rash, anaphylactic shock, photosensitivity, excessive perspiration and chills.

Cardiovascular System: Hypotension, headache, palpitations, tachycardia, extrasystoles.

Hematologic System: Hemolytic anemia, thrombocytopenia, agranulocytosis.

Nervous System: Sedation, sleepiness, dizziness, disturbed coordination, fatigue, confusion, restlessness, excitation, anxiety, nervousness, tremor, irritability, insomnia, euphoria, paresthesias, blurred vision, diplopia, vertigo, tinnitus, acute labyrinthitis, hysteria, neuritis, convulsions, CNS depression, hallucination.

G.I. System: Epigastric distress, anorexia, nausea, vomiting, diarrhea, constipation.

G.U. System: Urinary frequency, difficult urination, urinary retention, early menses.

Respiratory System: Thickening of bronchial secretions, tightness of chest and wheezing, nasal stuffiness, respiratory depression.

DRUG ABUSE AND DEPENDENCE

Like other medications containing a narcotic, Triacin-C is controlled by the Drug Enforcement Administration. It is classified under Schedule V.

Codeine can produce drug dependence of the morphine type, and therefore it has a potential for being abused. Psychic dependence, physical dependence and tolerance may develop on repeated administration.

The dependence liability of codeine has been found to be too small to permit a full definition of its characteristics. Studies indicate that addiction to codeine is extremely uncommon and requires very high parenteral doses.

When dependence on codeine occurs at therapeutic doses, it appears to require from one to two months to develop, and withdrawal symptoms are mild. Most patients on long-term oral codeine therapy show no signs of physical dependence upon abrupt withdrawal.

OVERDOSAGE

Since Triacin-C is comprised of three pharmacologically different compounds, it is difficult to predict the exact manifestation of symptoms in a given individual. Reaction to an overdosage of this product may vary from CNS depression to stimulation. A detailed description of symptoms which are likely to appear after ingestion of an excess of the individual components follows:

Overdosage with codeine can cause transient euphoria, drowsiness, dizziness, weariness, diminution of sensitivity, loss of sensation, vomiting, transient excitement in children, and occasionally in adult women, miosis progressing to nonreactive pinpoint pupils, itching sometimes with skin rashes and urticaria and clammy skin with mottled cyanosis. In more severe cases, muscular relaxation with depressed or absent superficial and deep reflexes and a positive Babinski sign may appear. Marked slowing of the respiratory rate with inadequate pulmonary ventilation and consequent cyanosis may occur. Terminal signs include shock, pulmonary edema, hypostatic or aspiration pneumonia and respiratory arrest, with death occurring within 6-12 hours following ingestion.

Overdoses of antihistamines may cause hallucinations, convulsions, or possibly death, especially in infants and children. Antihistamines are more likely to cause dizziness, sedation, and hypotension in elderly patients.

Overdosage with triprolidine may produce reactions varying from depression to stimulation of the Central Nervous System (CNS); the latter is particularly likely in children. Atropine-like signs and symptoms (dry mouth, fixed dilated pupils, flushing, tachycardia, hallucinations, convulsions, urinary retention, cardiac arrhythmias and coma) may occur.

Overdosage with pseudoephedrine can cause excessive CNS stimulation resulting in excitement, nervousness, anxiety, tremor, restlessness and insomnia. Other effects include tachycardia, hypertension, pallor, mydriasis, hyperglycemia and urinary retention. Severe overdosage may cause tachypnea or hyperpnea, hallucinations, convulsions, or delirium, but in some individuals there may be CNS depression with somnolence, stupor or respiratory depression. Arrhythmias (including ventricular fibrillation) may lead to hypotension and circulatory collapse. Severe hypokalemia can occur, probably due to compartmental shift rather than depletion of potassium. No organ damage or significant metabolic derangement is associated with pseudoephedrine overdosage.

The toxic plasma concentration of codeine is not known with certainty. Experimental production of mild to moderate CNS depression in healthy, nontolerant subjects occurs at plasma concentrations of 0.5-1.9µg/mL when codeine is given by intravenous infusion. The single lethal dose of codeine in adults is estimated to be from 0.5 to 1.0 gram. It is also estimated that 5 mg/kg could be fatal in children.

The LD50 (single, oral dose) of triprolidine is 163 to 308 mg/kg in the mouse (depending upon strain) and 840 mg/kg in the rat.

Insufficient data are available to estimate the toxic and lethal doses of triprolidine in humans. No reports of acute poisoning with triprolidine have appeared.

The LD50 (single, oral dose) of pseudoephedrine is 726 mg/kg in the mouse, 2206 mg/kg in the rat and 1177 mg/kg in the rabbit. The toxic and lethal concentrations in human biologic fluids are not known. Excretion rates increase with urine acidification and decrease with alkalinization. Few reports of toxicity due to pseudoephedrine have been published and no case of fatal overdosage is known.

Therapy, if instituted within 4 hours of overdosage, is aimed at reducing further absorption of the drug. In the conscious patient, vomiting should be induced even though it may have occurred spontaneously. If vomiting cannot be induced, gastric lavage is indicated. Adequate precautions must be taken to protect against aspiration, especially in infants and children. Charcoal slurry or other suitable agents should be instilled into the stomach after vomiting or lavage. Saline cathartics or milk of magnesia may be of additional benefit.

In the unconscious patient, the airway should be secured with a cuffed endotracheal tube before attempting to evacuate the gastric contents. Intensive supportive and nursing care is indicated, as for any comatose patient.

If breathing is significantly impaired, maintenance of an adequate airway and mechanical support of respiration is the most effective means of providing adequate oxygenation.

Hypotension is an early sign of impending cardiovascular collapse and should be treated vigorously. Do not use CNS stimulants. Convulsions should be controlled by careful administration of diazepam or short-acting barbiturate, repeated as necessary. Physostigmine may be also considered for use in controlling centrally mediated convulsions.

Ice packs and cooling sponge baths, not alcohol, can aid in reducing the fever commonly seen in children.

For codeine, continuous stimulation that arouses, but does not exhaust, the patient is useful in preventing coma. Continuous or intermittent oxygen therapy is usually indicated, while naloxone is useful as a codeine antidote. Close nursing care is essential.

Saline cathartics, such as milk of magnesia, help to dilute the concentration of the drugs in the bowel by drawing water into the gut, thereby hastening drug elimination.

Adrenergic receptor blocking agents are antidotes to pseudoephedrine. In practice, the most useful is the beta-blocker propranolol, which is indicated when there are signs of cardiac toxicity.

There are no specific antidotes to triprolidine. Histamine should not be given.

Pseudoephedrine and codeine are theoretically dialyzable, but the procedures have not been clinically established.

In severe cases of overdosage, it is essential to monitor both the heart (by electrocardiograph) and plasma electrolytes and to give intravenous potassium as indicated by these continuous controls. Vasopressors may be used to treat hypotension, and excessive CNS stimulation may be counteracted with parenteral diazepam. Stimulants should not be used.

DOSAGE AND ADMINISTRATION

DOSAGE SHOULD BE INDIVIDUALIZED ACCORDING TO THE NEEDS AND RESPONSE OF THE PATIENT.

Usual Dose: | Teaspoonfuls (5 mL)
Adults and children 12 years and older | 2 teaspoonfuls (10 mL) every 4 to 6 hours, not to exceed 8 teaspoonfuls (40 mL) in 24 hours.
Children 6 to under 12 years | 1 teaspoonful (5 mL) every 4 to 6 hours, not to exceed 4 teaspoonfuls (20 mL) in 24 hours.
Children 2 to under 6 years | ½ teaspoonful (2.5 mL) every 4 to 6 hours, not to exceed 2 teaspoonfuls

HOW SUPPLIED

Triacin-C, is supplied in a colorless, caramel flavored vehicle in 16 fl oz pint (473 mL) size bottles.

Each 5 mL (one teaspoonful) of syrup for oral administration contains:

Codeine Phosphate……10 mg

WARNING: May be habit forming.

Triprolidine Hydrochloride……1.25 mg

Pseudoephedrine Hydrochloride……30 mg

Alcohol 4.3%.

Inactive ingredients: sodium benzoate, methylparaben, sodium saccharin, sorbitol, glycerin, citric acid, sodium citrate, caramel flavor and USP purified water.

Store at controlled room temperature 20°to 25°C (68° to 77°F) [See USP Controlled Room Temperature.].

Dispense in a tight, light-resistant container as defined in the USP.

Rx Only.

Manufactured for

STI Pharma LLC

Langhorne, PA 19047

Rev 07/15

PRINCIPAL DISPLAY PANEL - 473ml (1 Pint Bottle)

NDC 54879-005-16

TRIACIN-C